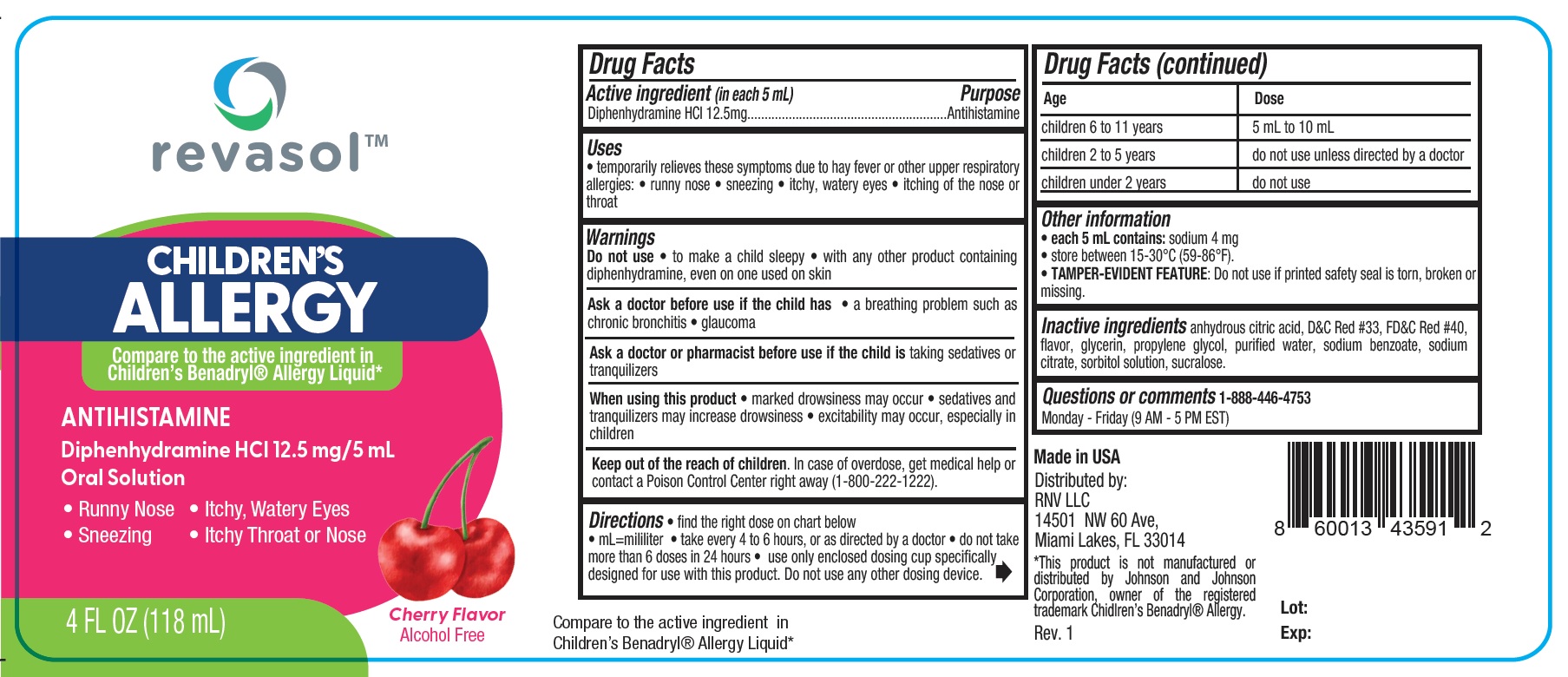 DRUG LABEL: REVASOL CHILDRENS ALLERGY
NDC: 84379-286 | Form: LIQUID
Manufacturer: Rnv LLC
Category: otc | Type: HUMAN OTC DRUG LABEL
Date: 20250326

ACTIVE INGREDIENTS: DIPHENHYDRAMINE HCL 12.5 mg/5 mL
INACTIVE INGREDIENTS: WATER; SUCRALOSE; SORBITOL SOLUTION 70%; SODIUM BENZOATE; PROPYLENE GLYCOL; SODIUM CITRATE; D&C RED NO. 33; MENTHOL; FD&C RED NO. 40; GLYCERIN; ANHYDROUS CITRIC ACID

REVASOL CHILDRENS ALLERGY

Active ingredient (in each 5 mL) Purpose
Diphenhydramine HCl 12.5mg..........................................................Antihistamine

Purpose

Antihistamine

Uses
• temporarily relieves these symptoms due to hay fever or other upper respiratory allergies:

• runny nose • sneezing • itchy, watery eyes • itching of the nose or throat

Warnings

Do not use • to make a child sleepy • with any other product containing diphenhydramine, even on one used on skin

Ask a doctor before use if the child has

• a breathing problem such as chronic bronchitis • glaucoma

Ask a doctor or pharmacist before use if the child is taking sedatives or tranquilizers

When using this product

• marked drowsiness may occur • sedatives and tranquilizers may increase drowsiness • excitability may occur, especially in children

KEEP OUT OF REACH OF CHILDREN

Keep out of the reach of children. In case of overdose, get medical help or contact a Poison Control Center right away (1-800-222-1222).

Directions

• find the right dose on chart below
• mL=mililiter • take every 4 to 6 hours, or as directed by a doctor • do not take more than 6 doses in 24 hours • use only enclosed dosing cup specifically designed for use with this product. Do not use any other dosing device.

Age | Dose
children 6 to 11 years | 5 mL to 10 mL
children 2 to 5 years | do not use unless directed by a doctor
children under 2 years | do not use

Other information
• each 5 mL contains: sodium 4 mg
• store between 15-30°C (59-86°F).
• TAMPER-EVIDENT FEATURE: Do not use if printed safety seal is torn, broken or missing.

Inactive ingredients

anhydrous citric acid, D&C Red #33, FD&C Red #40, flavor, glycerin, propylene glycol, purified water, sodium benzoate, sodium
citrate, sorbitol solution, sucralose.

Questions or comments 1-888-446-4753
Monday - Friday (9 AM - 5 PM EST)